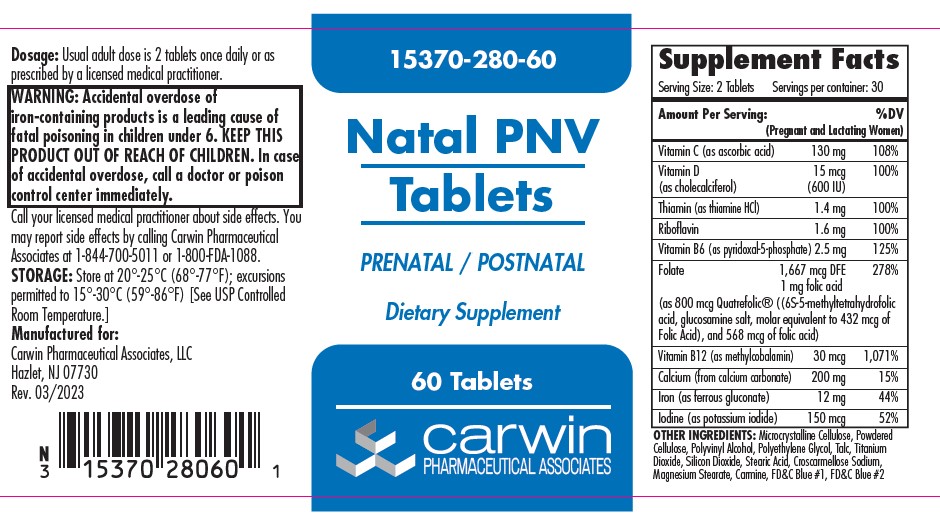 DRUG LABEL: Natal PNV
NDC: 15370-280 | Form: TABLET, FILM COATED
Manufacturer: Carwin Pharmaceutical Associatates, LLC
Category: other | Type: DIETARY SUPPLEMENT
Date: 20230504

ACTIVE INGREDIENTS: ASCORBIC ACID 130 mg/2 1; CHOLECALCIFEROL 15 ug/2 1; THIAMINE HYDROCHLORIDE 1.4 mg/2 1; RIBOFLAVIN 1.6 mg/2 1; PYRIDOXAL PHOSPHATE ANHYDROUS 2.5 mg/2 1; LEVOMEFOLATE GLUCOSAMINE 800 ug/2 1; FOLIC ACID 568 ug/2 1; METHYLCOBALAMIN 30 ug/2 1; CALCIUM CARBONATE 200 mg/2 1; FERROUS GLUCONATE 12 mg/2 1; POTASSIUM IODIDE 150 ug/2 1
INACTIVE INGREDIENTS: CELLULOSE, MICROCRYSTALLINE; POWDERED CELLULOSE; POLYVINYL ALCOHOL, UNSPECIFIED; POLYETHYLENE GLYCOL, UNSPECIFIED; TALC; TITANIUM DIOXIDE; SILICON DIOXIDE; STEARIC ACID; CROSCARMELLOSE SODIUM; MAGNESIUM STEARATE; CARMINIC ACID; FD&C BLUE NO. 1; FD&C BLUE NO. 2

Natal PNV Tablets

HEALTH CLAIM

Dispensed by Prescription

STATEMENT OF IDENTITY

Serving Size: 2 tablets Servings per container: 30

Amount Per Serving (Pregnant and Lactating Women) %DV

Vitamin C (as ascorbic acid) 130 mg 108%

Vitamin D (as cholecalciferol) 15 mg (600 U) 100%

Thiamin (as thiamin HCl) 1.4 mg 100%

Riboflavin 1.6 mg 100%

Vitamin B6 (as pyridoxol-5-phosphate) 2.5 mg 125%

Folate 1667 mcg, 1 mg folic acid 278% (as 800 mcg Quatrefolic® ((6S-5-methyltetrafolic acid, glucosamine salt, molar equivalent to 432 mcg Folic Acid), and 568 mcg of folic acid)

Vitamin B12 (as methylcobalomin) 30 mcg 1,071%

Calcium (from calcium carbonate) 200 mg 15%

Iron (as ferrous gluconate) 12 mg 44%

Iodine (as potassium iodide) 150 mcg 52%

OTHER INGREDIENTS: Microcrystalline Cellulose, Powdered Cellulose, Polyvinyl Alcohol, Polyethylene Glycol, Talc, Titanium Dioxide, Silicon Dioxide, Stearic Acid, Croscarmelose Sodium, Magnesium Stearate, Carmine, FD&C Blue #1, FD&C Blue #2

DESCRIPTION

Natal PNV Tablets is a prescription dietary supplement for use throughout pregnancy, during the postnatal period for both lactating and non-lactating mothers, and throughout the childbearing years. Natan PNV Tablets may be useful in improving the nutritional status of women prior to conception.

CONTRADINDICATIONS

Natal PNV Tablets are contraindicated in patients with a known hypersensitivity to any of the ingredients. Do not take this product if you are presently taking mineral oil, unless directed by a doctor.

WARNING

Accidental overdose of iron-containing products is a leading cause of fatal poisoning in children under 6. KEEP THIS AND ALL DRUGS OUT OF THE REACH OF CHILDREN. In case of accidental overdose, call a doctor or poison control center immediately.

ADVERSE REACTIONS

Allergic sensitization has been reported following both oral and parenteral administration of folic acid. You may report side effects by calling Carwin Pharmaceutical Associates at 1-844-700-5011 or the FDA by calling 1-800-FDA-1088.

DOSAGE AND ADMINISTRATION

Usual adult dose is 2 tablets taken orally once daily, or as prescribed by a licensed medical practitioner.

PRECAUTION:

Folic acid alone is improper therapy in the treatment of pernicious anemia and other megaloblastic anemias where vitamin B12 is deficient. Folic acid in doses above 0.1 mg daily may obscure pernicious anemia in that hematologic remission can occur while neurological manifestations progress. Natal PNV Tablets should only be used under the direction and supervision of a licensed medical practitioner.

SAFE HANDLING WARNING SECTION

Protect from heat, light and moisture.
Tamper Evident: Do not use if seal is broken or missing.

PACKAGE LABEL

Add image transcription here...